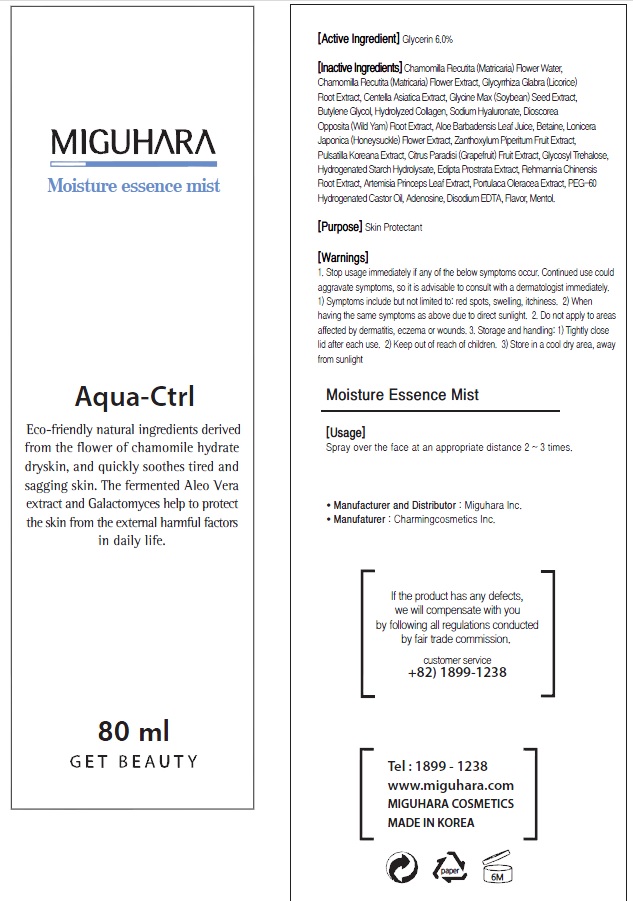 DRUG LABEL: Moisture Essence Mist
NDC: 70380-260 | Form: SPRAY
Manufacturer: MIGUHARA
Category: otc | Type: HUMAN OTC DRUG LABEL
Date: 20160223

ACTIVE INGREDIENTS: Glycerin 4.8 g/80 mL
INACTIVE INGREDIENTS: CHAMOMILE; Water

ACTIVE INGREDIENT

Active Ingredient: Glycerin 6.0%

INACTIVE INGREDIENT

Inactive Ingredients: Chamomilla Recutita (Matricaria) Flower, Water, Chamomilla Recutita (Matricaria) Flower Extract, Glycyrrhiza Glabra (Licorice) Root Extract, Centella Asiatica Extract, Glycine Max (Soybean) Seed Extract, Glycerin, Butylene Glycol, Hydrolyzed Collagen, Sodium Hyaluronate, Dioscorea Opposita (Wild Yam) Root Extract, Aloe Barbadensis Leaf Juice, Betaine, Lonicera Japonica (Honeysuckle) Flower Extract, Zanthoxylum Piperitum Fruit Extract, Pulsatilla Koreana Extract, Citrus Paradisi (Grapefruit) Fruit Extract, Glycosyl Trehalose, Hydrogenated Starch Hydrolysate, Eclipta Prostrata Extract, Rehmannia Chinensis Root Extract, Artemisia Princeps Leaf Extract, Portulaca Oleracea Extract, PEG-60 Hydrogenated Castor Oil, Adenosine, Disodium EDTA, Flavor, Mentol

PURPOSE

Purpose: Skin Protectant

WARNINGS

1. Stop usage immediately if any of the below symptoms occur. Continued use could aggravate symptoms, so it is advisable to consult with a dermatologist immediately. 1) Symptoms include but not limited to: red spots, swelling, itchiness. 2) When having the same symptoms as above due to direct sunlight. 2. Do not apply to areas affected by dermatitis, eczema or wounds. 3. Storage and handling: 1) Tightly close lid after each use. 2 Keep out of reach of children 3) Store in a cool dry area, away from sunlight

KEEP OUT OF REACH OF CHILDREN

Usage

Usage: Spray over the face at an appropriate distance 2 ~ 3 times.

Usage

Usage: Spray over the face at an appropriate distance 2 ~ 3 times.